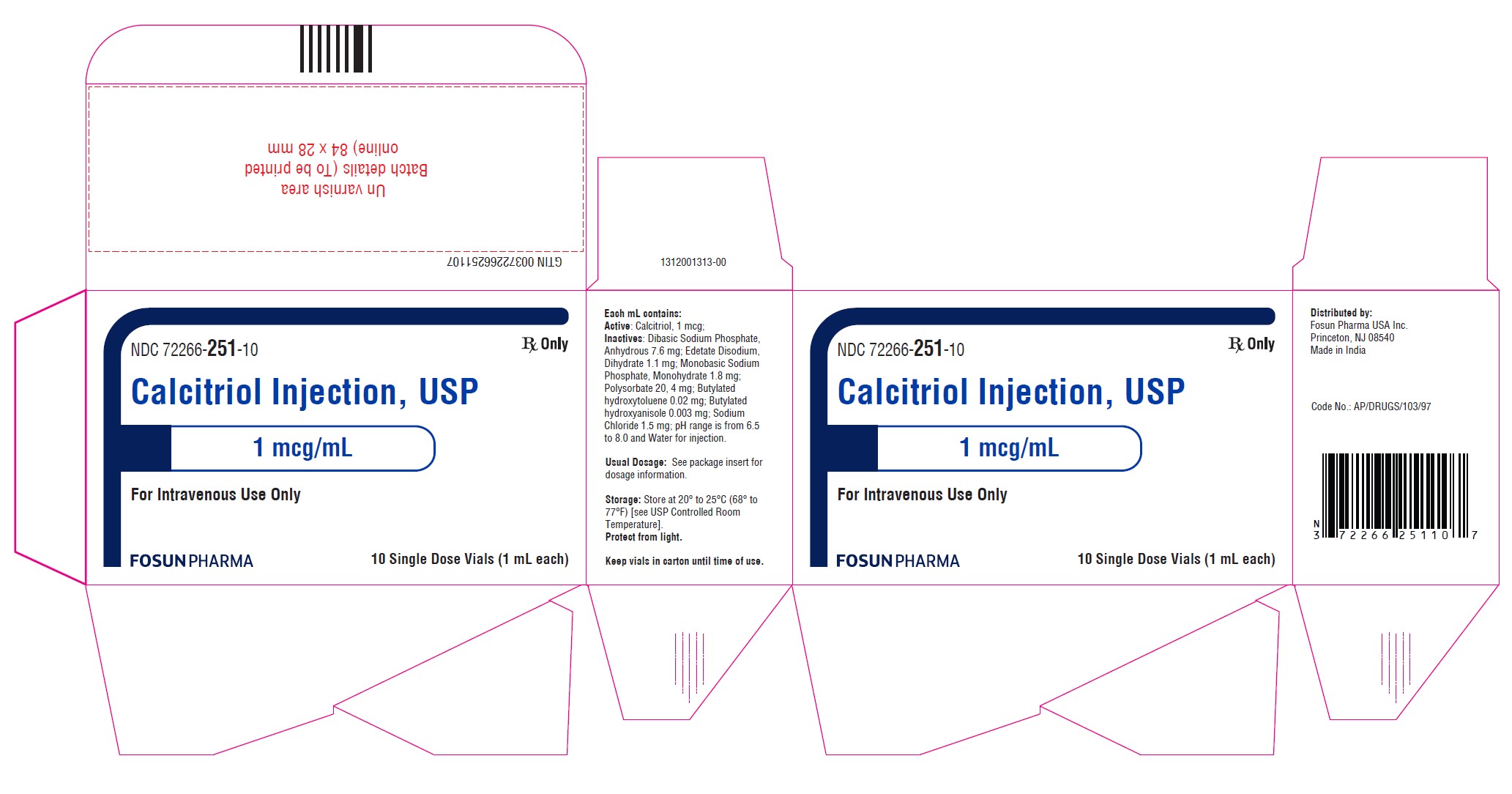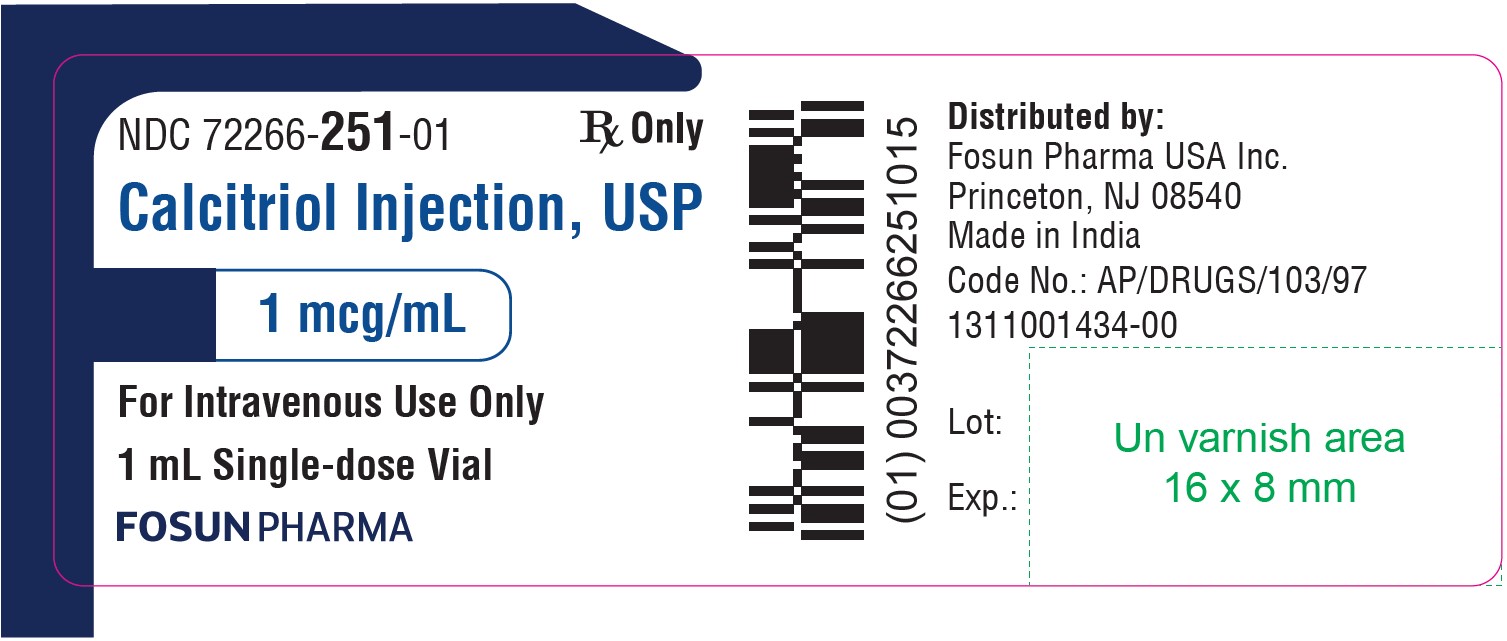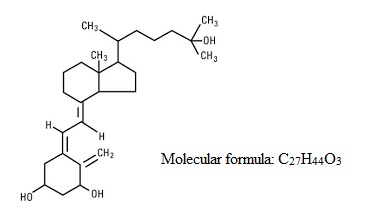 DRUG LABEL: Calcitriol
NDC: 72266-251 | Form: INJECTION
Manufacturer: FOSUN PHARMA USA INC
Category: prescription | Type: HUMAN PRESCRIPTION DRUG LABEL
Date: 20240502

ACTIVE INGREDIENTS: CALCITRIOL 1 ug/1 mL
INACTIVE INGREDIENTS: POLYSORBATE 20 4 mg/1 mL; BUTYLATED HYDROXYTOLUENE 0.02 mg/1 mL; BUTYLATED HYDROXYANISOLE 0.003 mg/1 mL; SODIUM CHLORIDE 1.5 mg/1 mL; SODIUM PHOSPHATE, DIBASIC, ANHYDROUS 7.6 mg/1 mL; SODIUM PHOSPHATE, MONOBASIC, MONOHYDRATE 1.8 mg/1 mL; EDETATE DISODIUM 1.1 mg/1 mL; WATER

CALCITRIOL INJECTION USP, 1 mcg/mL
Rx only

DESCRIPTION

Calcitriol injection is synthetically manufactured calcitriol and is available as a sterile, isotonic, clear, colorless to yellow, aqueous solution for intravenous injection. Calcitriol Injection, USP is available in 1 mL vials. Each 1 mL contains: Active: Calcitriol, 1 mcg. Inactives: Polysorbate 20, 4 mg; Dibasic Sodium Phosphate, Anhydrous 7.6 mg; Edetate Disodium, Dihydrate 1.1 mg; Monobasic Sodium Phosphate, Monohydrate 1.8 mg; Butylated hydroxyltoluene 0.02 mg; Butylated hydroxyl anisole 0.003 mg; Sodium Chloride 1.5 mg; pH Range is from 6.5 to 8.0 and Water for Injection.
Calcitriol is a crystalline compound which occurs naturally in humans. It is soluble in organic solvents but relatively insoluble in water. Calcitriol is chemically designated (5Z,7E)-9,10 secocholesta-5,7,10(19)-triene-1α,3β,25-triol and has the following structural formula:

The other names frequently used for calcitriol are 1α,25-dihydroxycholecalciferol,1α,25- dihydroxyvitamin D3,1,25-DHCC,1,25(OH)2D3and 1,25-diOHC.

CLINICAL PHARMACOLOGY

Calcitriol is the active form of vitamin D3(cholecalciferol). The natural or endogenous supply of vitamin D in man mainly depends on ultraviolet light for conversion of 7-dehydrocholesterol to vitamin D3in the skin. Vitamin D3must be metabolically activated in the liver and the kidney before it is fully active on its target tissues. The initial transformation is catalyzed by a vitamin D3-25-hydroxylase enzyme present in the liver, and the product of this reaction is 25-(OH)D3(calcifediol). The latter undergoes hydroxylation in the mitochondria of kidney tissue, and this reaction is activated by the renal 25-hydroxyvitamin D3-1-α-hydroxylase to produce 1,25-(OH)2D3(calcitriol), the active form of vitamin D3.
The known sites of action of calcitriol are intestine, bone, kidney and parathyroid gland. Calcitriol is the most active known form of vitamin D3 in stimulating intestinal calcium transport. In acutely uremic rats, calcitriol has been shown to stimulate intestinal calcium absorption. In bone, calcitriol, in conjunction with parathyroid hormone, stimulates resorption of calcium; and in the kidney, calcitriol increases the tubular reabsorption of calcium. In vitroand in vivostudies have shown that calcitriol directly suppresses secretion and synthesis of PTH. A vitamin D-resistant state may exist in uremic patients because of the failure of the kidney to adequately convert precursors to the active compound, calcitriol. Calcitriol when administered by bolus injection is rapidly available in the blood stream. Vitamin D metabolites are known to be transported in blood, bound to specific plasma proteins. The pharmacologic activity of an administered dose of calcitriol is about 3 to 5 days. Two metabolic pathways for calcitriol have been identified, conversion to 1,24,25-(OH)3D3and to calcitroic acid.

INDICATIONS AND USAGE

Calcitriol injection is indicated in the management of hypocalcemia in patients undergoing chronic renal dialysis. It has been shown to significantly reduce elevated parathyroid hormone levels. Reduction of PTH has been shown to result in an improvement in renal osteodystrophy.

CONTRAINDICATIONS

Calcitriol injection should not be given to patients with hypercalcemia or evidence of vitamin D toxicity.
Calcitriol injection is contraindicated in patients with previous hypersensitivity to calcitriol or any of its excipients.

WARNINGS

Since calcitriol is the most potent metabolite of vitamin D available, prescription-based doses of vitamin D and its derivatives should be withheld or used with caution during treatment to avoid the risk of hypercalcemia.
A non-aluminum phosphate-binding compound should be used to control serum phosphorous levels in patients undergoing dialysis.
Overdosage of any form of vitamin D is dangerous (see also OVERDOSAGE). Progressive hypercalcemia due to overdosage of vitamin D and its metabolites may be so severe as to require emergency attention. Chronic hypercalcemia can lead to generalized vascular calcification, nephrocalcinosis and other soft tissue calcification. The serum calcium times phosphate (Ca x P) product should not be allowed to exceed 70 mg^2/dL^2. Radiographic evaluation of suspect anatomical regions may be useful in the early detection of this condition.

PRECAUTIONS

General

Excessive dosage of calcitriol injection induces hypercalcemia and in some instances hypercalciuria; therefore, early in treatment during dosage adjustment, serum calcium and phosphorus should be determined at least twice weekly. Should hypercalcemia develop, the drug should be discontinued immediately.
Calcitriol injection should be given cautiously to patients on digitalis, because hypercalcemia in such patients may precipitate cardiac arrhythmias.

Information for the Patient

The patient and his or her parents should be informed about adherence to instructions about diet and calcium supplementation and avoidance of the use of unapproved non-prescription drugs, including magnesium-containing antacids. Patients should also be carefully informed about the symptoms of hypercalcemia (see ADVERSE REACTIONS).

Essential Laboratory Tests

Serum calcium, phosphorus, magnesium and alkaline phosphatase and 24-hour urinary calcium and phosphorus should be determined periodically. During the initial phase of the medication, serum calcium and phosphorus should be determined more frequently (twice weekly).
Adynamic bone disease may develop if PTH levels are suppressed to abnormal levels. If biopsy is not being done for other (diagnostic) reasons, PTH levels may be used to indicate the rate of bone turnover. If PTH levels fall below recommended target range (1.5 to 3 times the upper limit of normal), in patients treated with calcitriol injection, the calcitriol injection dose should be reduced or therapy discontinued. Discontinuation of calcitriol therapy may result in rebound effect, therefore, appropriate titration downward to a maintenance dose is recommended.

Drug Interactions

Concomitant use of magnesium-containing preparations should be used with caution or avoided since such use may lead to the development of hypermagnesemia.
Corticosteroids with glucocorticoid activity may counteract the bone and mineral metabolism effects of vitamin D analogues.
Cytochrome P450 enzyme-inducing anticonvulsants such as carbamazepine, phenobarbital and phenytoin may reduce the effects of vitamin D because they increase vitamin D catabolism.

Carcinogenesis, Mutagenesis, Impairment of Fertility

Long-term studies in animals have not been conducted to evaluate the carcinogenic potential of calcitriol injection. Calcitriol was not mutagenic in vitroin the Ames Test nor was oral calcitriol genotoxic in vivoin the Mouse Micronucleus Test. No significant effects on fertility and/or general reproductive performances were observed in a Segment I study in rats using oral calcitriol at doses of up to 0.3 mcg/kg.

Pregnancy

Teratogenic Effects

Pregnancy Category C

Calcitriol has been found to be teratogenic in rabbits when given orally at doses of 0.08 and 0.3 mcg/kg. All 15 fetuses in 3 litters at these doses showed external and skeletal abnormalities. However, none of the other 23 litters (156 fetuses) showed external and skeletal abnormalities compared with controls. Teratogenicity studies in rats at doses up to 0.45 mcg/kg orally showed no evidence of teratogenic potential. There are no adequate and well-controlled studies in pregnant women. Calcitriol injection should be used during pregnancy only if the potential benefits justifies the potential risk to the fetus.

Nonteratogenic Effects

In the rabbit, oral dosages of 0.3 mcg/kg/day administered on days 7 to 18 of gestation resulted in 19% maternal mortality, a decrease in mean fetal body weight and a reduced number of newborns surviving to 24 hours. A study of the effects on orally administered calcitriol on peri- and postnatal development in rats resulted in hypercalcemia in the offspring of dams given calcitriol at doses of 0.08 or 0.3 mcg/kg/day, hypercalcemia and hypophosphatemia in dams given calcitriol at a dose of 0.08 or 0.3 mcg/kg/day and increased serum urea nitrogen in dams given calcitriol at a dose of 0.3 mcg/kg/day. In another study in rats, maternal weight gain was slightly reduced at an oral dose of 0.3 mcg/kg/day administered on days 7 to 15 of gestation.
The offspring of a woman administered oral calcitriol at 17 to 36 mcg/day during pregnancy manifested mild hypercalcemia in the first 2 days of life which returned to normal at day 3.

Nursing Mothers

It is not known whether this drug is excreted in human milk. Because many drugs are excreted in human milk and because of the potential for serious adverse reactions in nursing infants from calcitriol, a decision should be made whether to discontinue nursing or to discontinue the drug, taking into account the importance of the drug to the mother.

Pediatric Use

The safety and effectiveness of calcitriol injection were examined in a 12-week randomized, doubleblind, placebo-controlled study of 35 pediatric patients, aged 13 to 18 years, with end-stage renal disease on hemodialysis. Sixty-six percent of the patients were male, 57% were African-American, and nearly all had received some form of vitamin D therapy prior to the study. The initial dose of calcitriol was 0.5 mcg, 1 mcg, or 1.5 mcg, 3 times per week, based on baseline iPTH level of less than 500 pg/mL, 500-1000 pg/mL, or greater than 1000 pg/mL, respectively. The dose of calcitriol was adjusted in 0.25 mcg increments based on the levels of serum iPTH, calcium, and Ca x P. The mean baseline levels of iPTH were 769 pg/mL for the 16 calcitriol-treated patients and 897 pg/mL for the 19 placebo-treated subjects. The mean weekly dose of calctiriol ranged from 1 mcg to 1.4 mcg. In the primary efficacy analysis, 7 of 16 (44%) subjects in the calcitriol group had 2 consecutive 30% decreases from baseline iPTH compared with 3 to 19 (16%) patients in the placebo group (95% CI for the difference between groups -6%, 62%). One calcitriol-treated patient experienced transient hypercalcemia (>11.0 mg/dL), while 6 of 16 (38%) calcitriol-treated patients vs. 2 of 19 (11%) placebo-treated patients experienced Ca x P>75.

Geriatric Use

Clinical studies of calcitriol injection did not include sufficient numbers of subjects aged 65 and over to determine whether they respond differently from younger subjects. Other reported clinical experience has not identified differences in responses between the elderly and younger patients. In general, dose selection for an elderly patient should be cautious, usually starting at the low end of the dosage range, reflecting greater frequency of decreased hepatic, renal, or cardiac function, and of concomitant disease or other drug therapy.

ADVERSE REACTIONS

Adverse effects of calcitriol injection are, in general, similar to those encountered with excessive vitamin D intake. The early and late signs and symptoms of vitamin D intoxication associated with hypercalcemia include:

Early

Weakness, headache, somnolence, nausea, vomiting, dry mouth, constipation, muscle pain, bone pain, metallic taste, anorexia, abdominal pain and epigastric discomfort.

Late

Polyuria, polydipsia, anorexia, weight loss, nocturia, conjunctivitis (calcific) pancreatitis, photophobia, rhinorrhea, pruritus, hyperthermia, decreased libido, elevated BUN, albuminuria, hypercholesterolemia, elevated SGOT and SGPT, ectopic calcification, hypertension, cardiac arrhythmias, nephrocalcinosis, sensory disturbance, dehydration, apathy, and, rarely, overt psychosis.
Occasional mild pain on injection has been observed.

Post-Marketing Experience

Rare cases of hypersensitivity reactions have been reported, including anaphylaxis.

To report SUSPECTED ADVERSE REACTIONS, contact Fosun Pharma USA Inc. at 1-866-611-3762 or FDA at 1-800-FDA-1088 or www.fda.gov/medwatch.

OVERDOSAGE

Administration of calcitriol injection to patients in excess of their requirements can cause hypercalcemia, hypercalciuria and hyperphosphatemia. High intake of calcium and phosphate concomitant with calcitriol injection may lead to similar abnormalities (see WARNINGS, PRECAUTIONSand ADVERSE REACTIONS).

Treatment of Hypercalcemia and Overdosage in Patients on Hemodialysis

General treatment of hypercalcemia (greater than 1 mg/dL above the upper limit of normal range) consists of immediate discontinuation of calcitriol injection therapy, institution of a low calcium diet and withdrawal of calcium supplements. Serum calcium levels should be determined daily until normocalcemia ensues. Hypercalcemia usually resolves in two to seven days. When serum calcium levels have returned to within normal limits, Calcitriol Injection therapy may be reinstituted at a dose 0.5 mcg less than prior therapy. Serum calcium levels should be obtained at least twice weekly after all dosage changes.
Persistent or markedly elevated serum calcium levels may be corrected by dialysis against a calciumfree dialysate.

Treatment of Accidental Overdosage of Calcitriol Injection

The treatment of acute accidental overdosage of calcitriol injection should consist of general supportive measures. Serial serum electrolyte determinations (especially calcium), rate of urinary calcium excretion and assessment of electrocardiographic abnormalities due to the hypercalcemia should be obtained. Such monitoring is critical in patients receiving digitalis. Discontinuation of supplemental calcium and low calcium diet are also indicated in accidental overdosage. Due to the relatively short duration of the pharmacological action of calcitriol, further measures are probably unnecessary. Should, however, persistent and markedly elevated serum calcium levels occur, there are a variety of therapeutic alternatives which may be considered, depending on the patients' underlying condition. These include the use of drugs such as phosphates and corticosteroids as well as measures to induce an appropriate forced diuresis. The use of peritoneal dialysis against a calcium-free dialysate has also been reported.

DOSAGE AND ADMINISTRATION

Calcitriol injection is for intravenous injection only.
The optimal dose of calcitriol injection must be carefully determined for each patient.
The effectiveness of calcitriol injection therapy is predicated on the assumption that each patient is receiving an adequate and appropriate daily intake of calcium. The RDA for calcium in adults is 800 mg. To ensure that each patient receives an adequate daily intake of calcium, the physician should either prescribe a calcium supplement or instruct the patient in proper dietary measures.
The recommended initial dose of Calcitriol Injection, depending on the severity of the hypocalcemia and/or secondary hyperparathyroidism, is 1 mcg (0.02 mcg/kg) to 2 mcg administered intravenously three times weekly, approximately every other day. Doses as small as 0.5 mcg and as large as 4 mcg three times weekly have been used as an initial dose. If a satisfactory response is not observed, the dose may be increased by 0.5 to 1 mcg at two to four week intervals. During this titration period, serum calcium and phosphorus levels should be obtained at least twice weekly. If hypercalcemia or a serum calcium times phosphate product greater than 70 is noted, the drug should be immediately discontinued until these parameters are appropriate. Then, the calcitriol injection dose should be reinitiated at a lower dose. Doses may need to be reduced as the PTH levels decrease in response to the therapy. Thus, incremental dosing must be individualized and commensurate with PTH, serum calcium and phosphorus levels. The following is a suggested approach in dose titration:

PTH Levels | Calcitriol Injection Dose
the same or increasing | increase
decreasing by < 30% | increase
decreasing by > 30%, < 60% | maintain
decreasing by > 60% | decrease
one and one-half to three times the upper limit of normal | maintain

Parenteral drug products should be inspected visually for particulate matter and discoloration prior to administration, whenever solution and container permit.
Discard unused portion.

How Supplied

Calcitriol Injection, USP is supplied in 1 mL fill in 2 mL vials containing 1 mcg.
NDC 72266-251-10 10 Single Dose Vials in one carton
Storage: Store at 20° to 25°C (68° to 77°F) [see USP Controlled Room Temperature].
Protect from light.
Distributed by:
Fosun Pharma USA Inc.
Princeton, NJ 08540
Made in India

May 2023

1313000926-00

PACKAGE LABEL.PRINCIPAL DISPLAY PANEL

Vial Label:
NDC 72266-251-01
Calcitriol Injection, USP
1 mcg/mL
For Intravenous Use Only
1 mL Single-dose Vial
Rx only

Carton Label:
NDC 72266-251-10

10 Single Dose Vials in one carton

Calcitriol Injection, USP
1 mcg/mL
For Intravenous Use Only
1 mL Single-dose Vial
Rx only